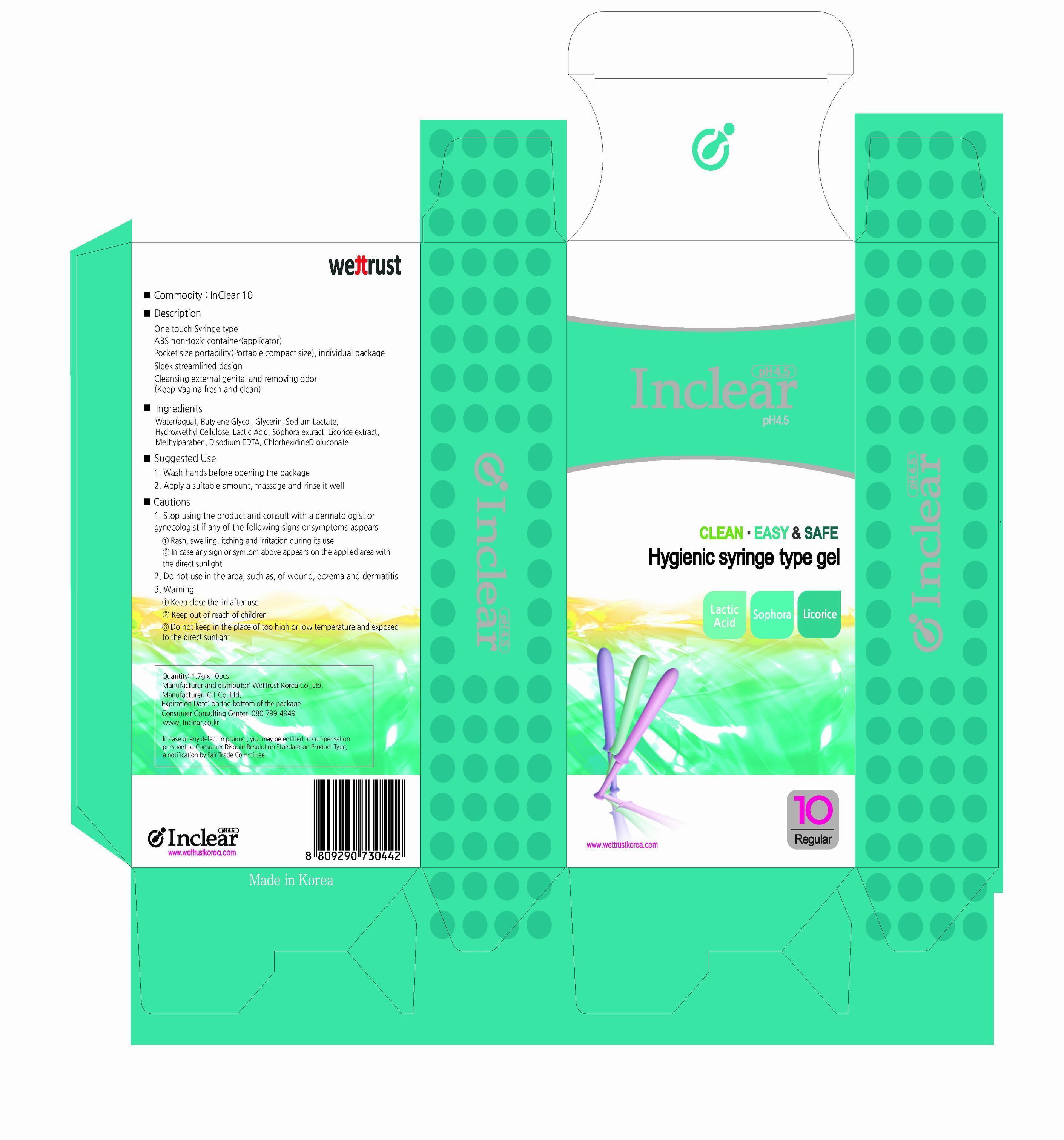 DRUG LABEL: Inclear
NDC: 59543-3001 | Form: GEL
Manufacturer: WeTTrust Korea Co., Ltd
Category: otc | Type: HUMAN OTC DRUG LABEL
Date: 20130729

ACTIVE INGREDIENTS: Glycerin 0.04 g/1 g
INACTIVE INGREDIENTS: WATER; BUTYLENE GLYCOL; SODIUM LACTATE; LACTIC ACID; EDETATE DISODIUM; METHYLPARABEN; GLYCYRRHIZA GLABRA

Drug Facts

ACTIVE INGREDIENT

glycerin

INACTIVE INGREDIENT

water, butylene glycol, sodium lactate, hydroxyethyl cellulose, lactic acid, sophora extract, licorice extract, methylparaben, disodium edta, chlorhexidine Digluconate

PURPOSE

cleansing external genital and revoving odor (keep vagina fresh and clean)

keep out of reach of the children

INDICATIONS AND USAGE

wash hands before opening the package
apply a suitable amount, massage and rinse it well

WARNINGS

- stop using the product and consult with a dermatologist or gynecologist if any of the following signs or symptoms appears
rash, swelling, itching and irritation during its use
in case any sign or symptom above appears on the applied area with the direct sunlight
- do not use in the area, such as, of wound, eczema and dermatitis

DOSAGE AND ADMINISTRATION

for vaginal use only